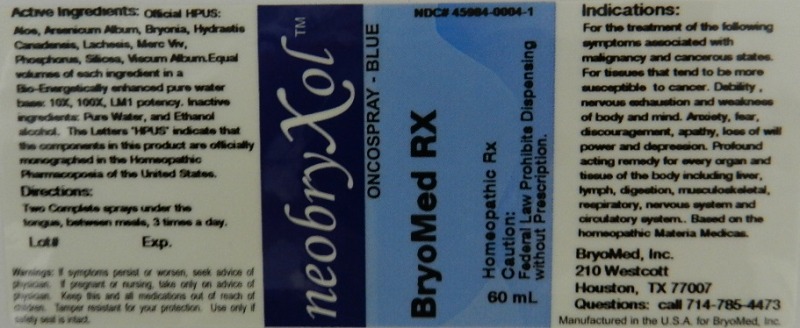 DRUG LABEL: Oncospray Blue
NDC: 45984-0004 | Form: LIQUID
Manufacturer: Bryomed Inc.
Category: homeopathic | Type: HUMAN PRESCRIPTION DRUG LABEL
Date: 20120309

ACTIVE INGREDIENTS: ALOE 10 [hp_X]/60 mL; ARSENIC TRIOXIDE 10 [hp_X]/60 mL; BRYONIA ALBA ROOT 10 [hp_X]/60 mL; GOLDENSEAL 10 [hp_X]/60 mL; LACHESIS MUTA VENOM 10 [hp_X]/60 mL; PHOSPHORUS 10 [hp_X]/60 mL; SILICON DIOXIDE 10 [hp_X]/60 mL; VISCUM ALBUM WHOLE 10 [hp_X]/60 mL; MERCURY 10 [hp_X]/60 mL
INACTIVE INGREDIENTS: WATER; ALCOHOL

Oncospray Blue

Active Ingredients

Official HPUS: Aloe socotrina, Arsenicum Album, Bryonia, Hydrastis canadensis, Lachesis mutus, Mercurius Vivus, Phosphorus, Silicea and Viscum album.

Reference image oncospray.jpg

Inactive Ingredients

Equal volumes of each ingredient in a Bio-Energetically enhanced pure water base: 10X, 100X and LM1 potency.

Inactive ingredients: Pure water and Ethanol Alcohol.

Reference image oncospray.jpg

Dosage and Administration

Directions: Two complete sprays under the tongue, between meals, 3 times a day.

Reference image oncospray.jpg

Purpose

Indications:

For the treatment of the following symptoms associated with malignancy and cancerous states.

- for tissues that tend to be more susceptible to cancer
- debility, nervous exhaustion and weakness of body and mind
- anxiety, fear, discouragement, apathy, loss of will power and depression
- profound acting remedy for every organ and tissue of the body including liver, lymph, digestion, musculoskeletal, respiratory, nervous system and circulatory system

Based on the homeopathic Materia Medicas.
Reference image oncospray.jpg

Warnings

Warnings: If symptoms persist or worsen, seek advice of physician. If pregnant or nursing, take only on advice of physician. Keep this and all medications out of reach of children.

Tamper resistant for your protection. Use only if safety seal is intact.

Caution: Federal law prohibits dispensing without prescription.

Reference image oncospray.jpg

KEEP OUT OF REACH OF CHILDREN

Keep this and all medications out of reach of children.

Indications and Usage

For the treatment of the following symptoms associated with malignancy and cancerous states. For tissues that tend to be more susceptible to cancer. Debility, nervous exhaustion and weakness of body and mind. Anxiety, fear, discouragement, apathy, loss of will power and depression. Profound acting remedy for every organ and tissue of the body including liver, lymph, digestion, musculoskeletal, respiratory, nervous system and circulatory system.

Based on the homeopathic Materia Medicas.
Reference image oncospray.jpg

PACKAGE LABEL

BryoMed, Inc.

210 Westcott

Houston TX 77007

Question call 714-785-4473